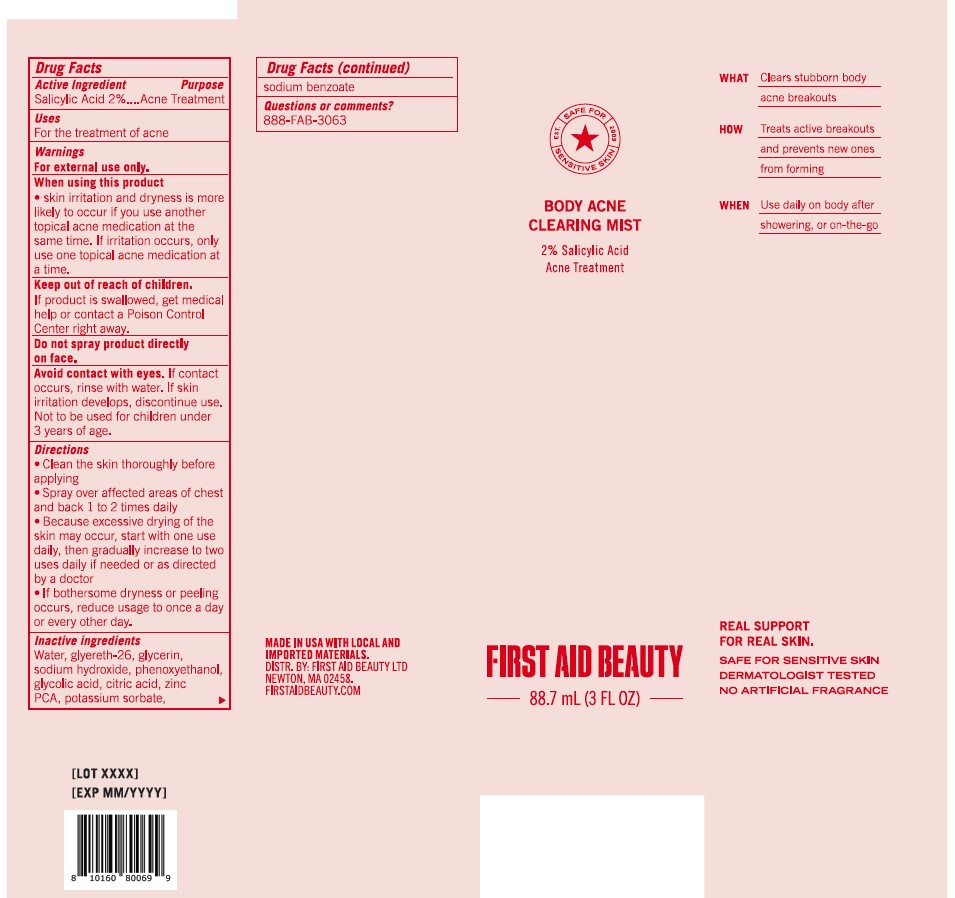 DRUG LABEL: First Aid Beauty Body Acne Clearing Mist
NDC: 84126-120 | Form: SPRAY
Manufacturer: The Procter & Gamble Manufacturing Company
Category: otc | Type: HUMAN OTC DRUG LABEL
Date: 20250522

ACTIVE INGREDIENTS: SALICYLIC ACID 2 g/100 mL
INACTIVE INGREDIENTS: SODIUM HYDROXIDE; PHENOXYETHANOL; POTASSIUM SORBATE; WATER; GLYCERIN; CITRIC ACID; SODIUM BENZOATE; GLYCOLIC ACID; GLYCERETH-26; ZINC PCA

First Aid Beauty Body Acne Clearing Mist

Drug Facts

Active ingredients

Salicylic Acid 2%

Purpose

Acne Treatment

Uses

- for the treatment of acne

Warnings

For external use only.

When using this product

- Skin irritation and dryness is more likely to occur if you use another topical acne medication at the same time. If irritation occurs, only use one topical acne medication at a time.

Keep out of reach of children. If swallowed, get medical help or contact a Poison Control Center right away.

WHEN USING

Do not spray product directly on face.

Avoid contact with eyes. If contact occurs, rinse with water. If skin irritation develops, discontinue use. Not to be used for children under 3 years of age.

Directions

- Clean the skin thoroughly before applying
- Spray over affected areas of chest and back 1 to 2 times daily.
- Because excessive drying of the skin may occur, start with one use daily, then gradually increase to two uses daily if needed or as directed by a doctor
- If bothersome dryness or peeling occurs, reduce usage to once a day or every other day.

INACTIVE INGREDIENT

Water, glycereth-26, glycerin, sodium hydroxide, phenoxyethanol, glycolic acid, citric acid, zinc PCA, potassium sorbate, sodium benzoate

Questions:

888-FAB-3063

MADE IN USA

FIRST AID BEAUTY LTD

NEWTON, MA 02458

WWW.FIRSTAIDBEAUTY.COM

PRINCIPAL DISPLAY PANEL - 22 mL carton

First Aid Beauty

Safe for sensitive skin

BODY ACNE CLEARING MIST

2% Salicylic Acid

Acne Treatment

88.7 mL (3 FL OZ)